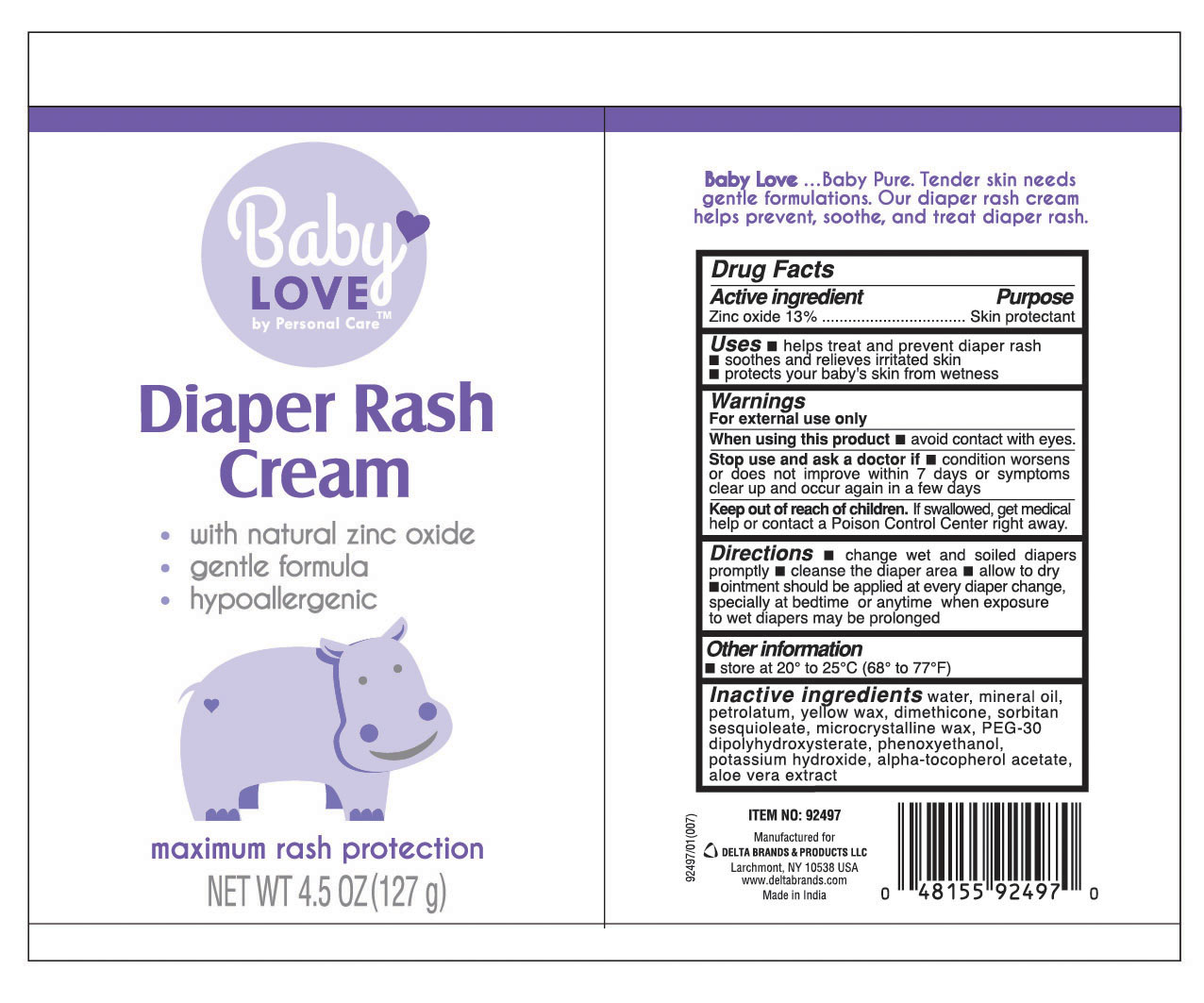 DRUG LABEL: Baby LOVE Personal CARE
NDC: 72133-321 | Form: CREAM
Manufacturer: Delta Brands & Products LLC
Category: otc | Type: HUMAN OTC DRUG LABEL
Date: 20180413

ACTIVE INGREDIENTS: ZINC OXIDE 13 g/100 g
INACTIVE INGREDIENTS: WATER; MINERAL OIL; MICROCRYSTALLINE WAX; PETROLATUM; YELLOW WAX; SORBITAN SESQUIOLEATE; DIMETHICONE; ALOE VERA LEAF; PEG-30 DIPOLYHYDROXYSTEARATE; PHENOXYETHANOL; POTASSIUM HYDROXIDE; ALPHA-TOCOPHEROL ACETATE

Drug Facts

Active Ingredient

Zinc oxide 13%

Purpose

Skin Protectant

Uses

■ helps treat and prevent diaper rash

■ soothes and relieves irritated skin

■ protects your baby's skin from wetness

Warnings

For external use only

When using this product

■ avoid contact with eyes

Stop use and ask a doctor if

■ condition worsens or does not improve within 7 days or symptoms clear up and occur again in a few days.

Keep out of reach of children

If swallowed, get medical help or contact a Poison Control Center right away

Directions

■ change wet and soiled diapers promptly ■ cleanse the diaper area ■ allow to dry ■ ointment should be applied at every diaper change, especially at bedtime or anytime when exposure to wet diapers may be prolonged

Other Information

■ store at 20º to 25ºC (68º to 77ºF)

Inactive Ingredients

water, mineral oil, petrolatum, yellow wax, dimethicone, sorbitan sesquioleate, microcrystalline wax, PEG-30 dipolyhydroxysterate, phenoxyethanol, potassium hydroxide, alpha-tocopherol acetate, aloe vera extract